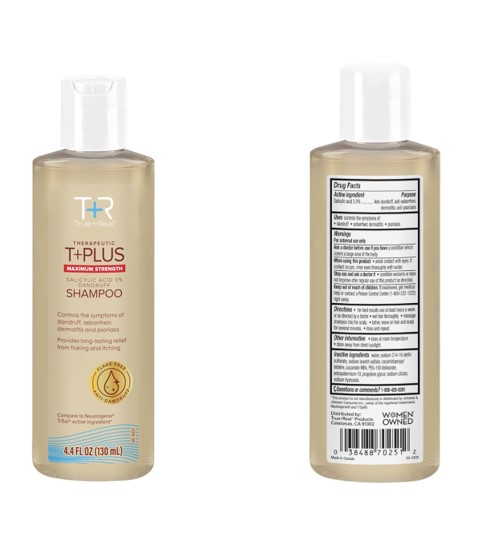 DRUG LABEL: Therapeutic TPlus Salicylic Acid
NDC: 67385-512 | Form: SHAMPOO
Manufacturer: Garcoa, Inc.
Category: otc | Type: HUMAN OTC DRUG LABEL
Date: 20260121

ACTIVE INGREDIENTS: SALICYLIC ACID 30 mg/1 mL
INACTIVE INGREDIENTS: Water; Sodium C14-16 Olefin Sulfonate; SODIUM LAURETH-3 SULFATE; Cocamidopropyl Betaine; COCO MONOETHANOLAMIDE; PEG-150 Distearate; POLYQUATERNIUM-10 (30000 MPA.S AT 2%); Propylene Glycol; SODIUM CITRATE, UNSPECIFIED FORM; Sodium Hydroxide

CVS Health® MAXIMUM STRENGTH Therapeutic Dandruff Shampoo
Anti-dandruff, anti-seborrheic dermatitis, anti-psoriasis

Drug Facts

Active ingredient

Salicylic acid 3.0%

Purpose

Anti-dandruff, anti-seborrheic dermatitis, anti-psoriasis

Uses

controls the symptom of:

- dandruff
- seborrheic dermatitis
- psoriasis

Warnings

For external use only.

Ask a doctor before use if you have a condition that covers a large area of the body.

When using this product

- avoid contact with the eyes. If contact occurs, rinse eyes thoroughly with water.

Stop use and ask a doctor if

- condition worsens or does not improve after regular use of this product as directed.

Keep out of reach of children. If swallowed, get medical help or contact a Poison Control Center (1-800-222-1222) right away.

Directions

- for best results use at least twice a week or as directed by a doctor.
- wet hair thoroughly.
- massage shampoo into the scalp.
- lather, leave on hair and scalp for several minutes.
- rinse and repeat.

Other information

- store at room temperature
- store away from direct sunlight

Inactive ingredients

water, sodium C14-16 olefin sulfonate, sodium laureth sulfate, cocamidopropyl betaine, cocamide MEA, PEG-150 distearate, polyquaternium-10, propylene glycol, sodium citrate, sodium hydroxide

Questions or comments?

1-800-426-9391

Distributed by:
True+Real Products

Calabasas, CA 91302

PRINCIPAL DISPLAY PANEL - 130 mL Bottle Carton

T+R

True+Real

THERAPEUTIC

T+PLUS

MAXIMUM STRENGTH

SALICYLIC ACID 3% DANDRUFF

SHAMPOO

Controls the symptoms of

dandruff, seborrheic

dermatitis, and psoriasis

Provides long-lasting relief from flaking and itching

FLAKE-FREE

ANTI-DANDRUFF

Compare to Neutrogena

T/Sal active ingredient

4.5 FL OZ (130 mL)

TPlus